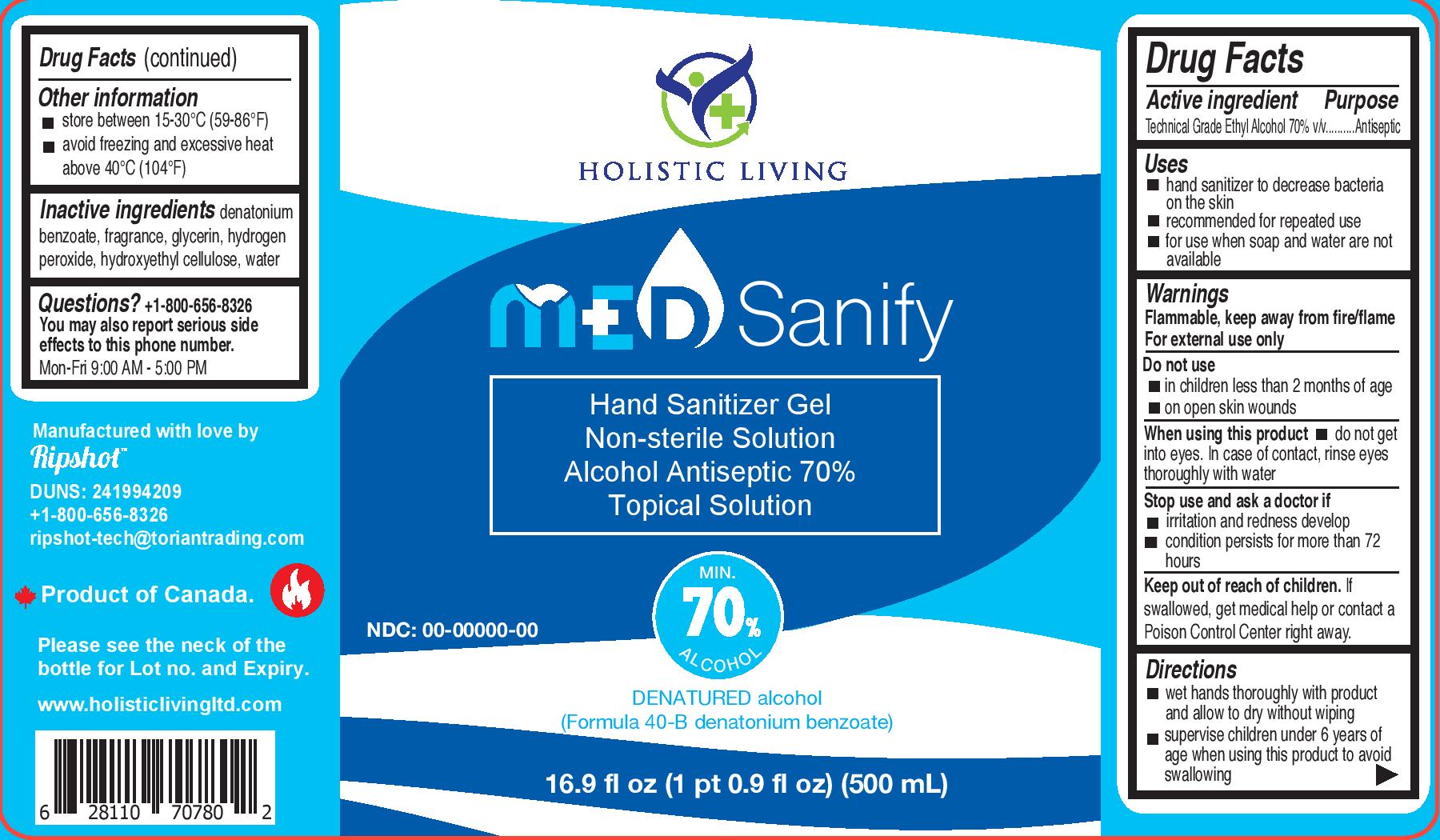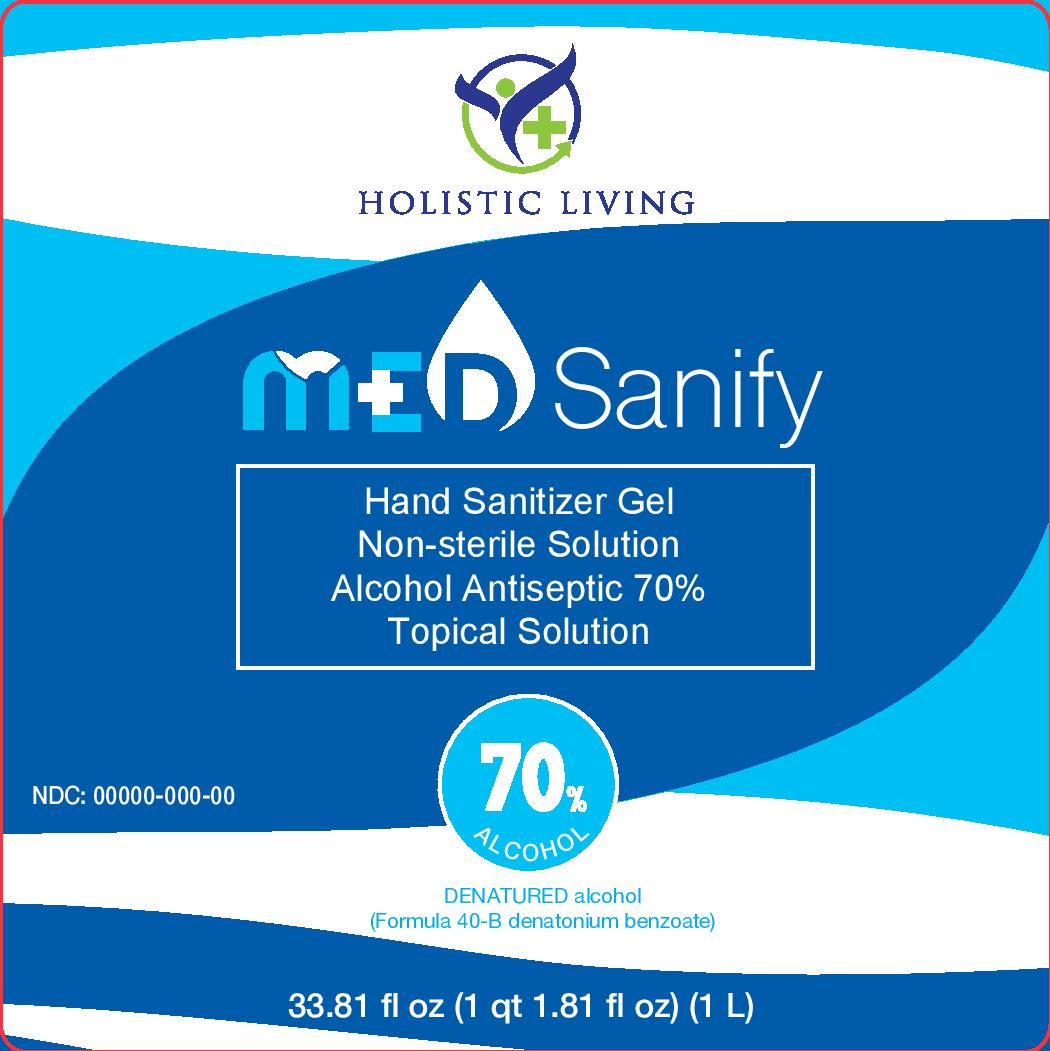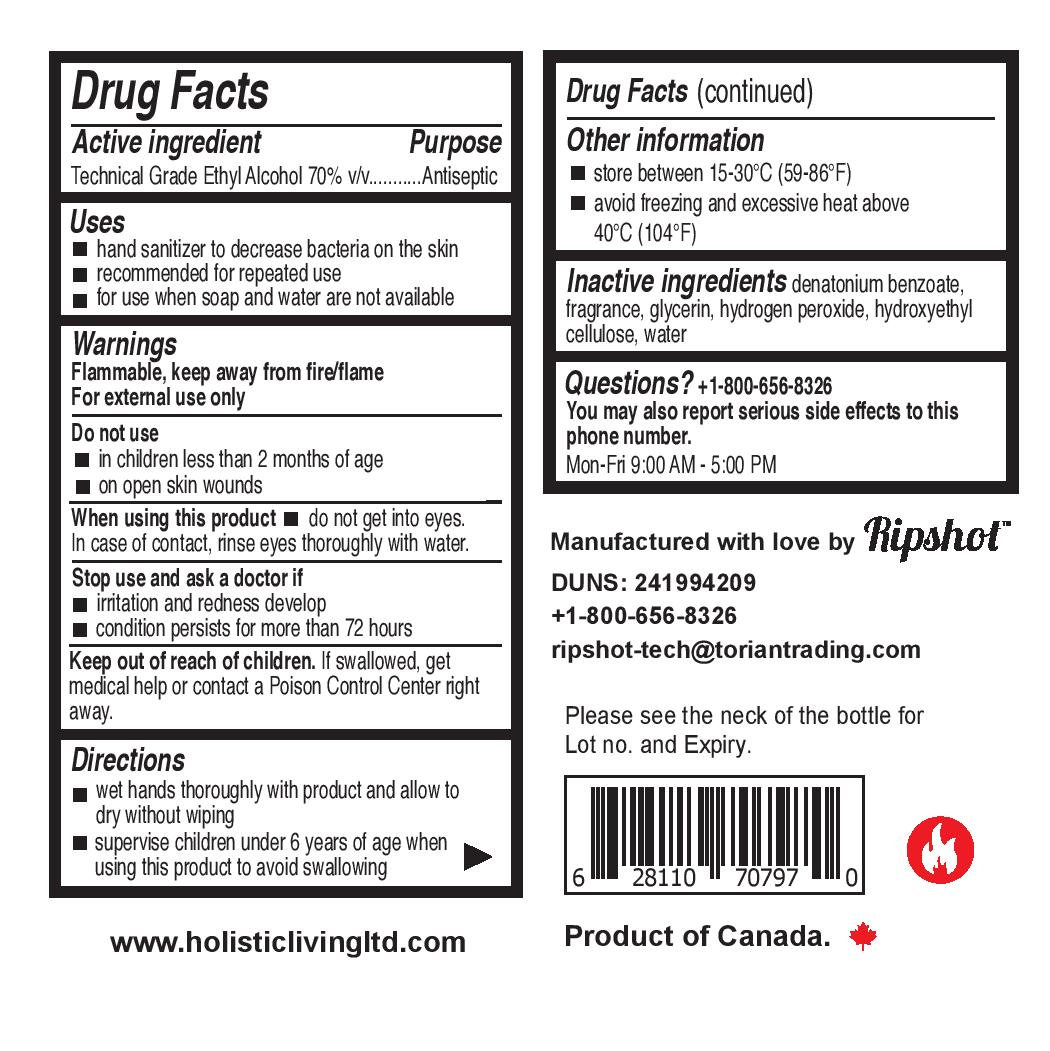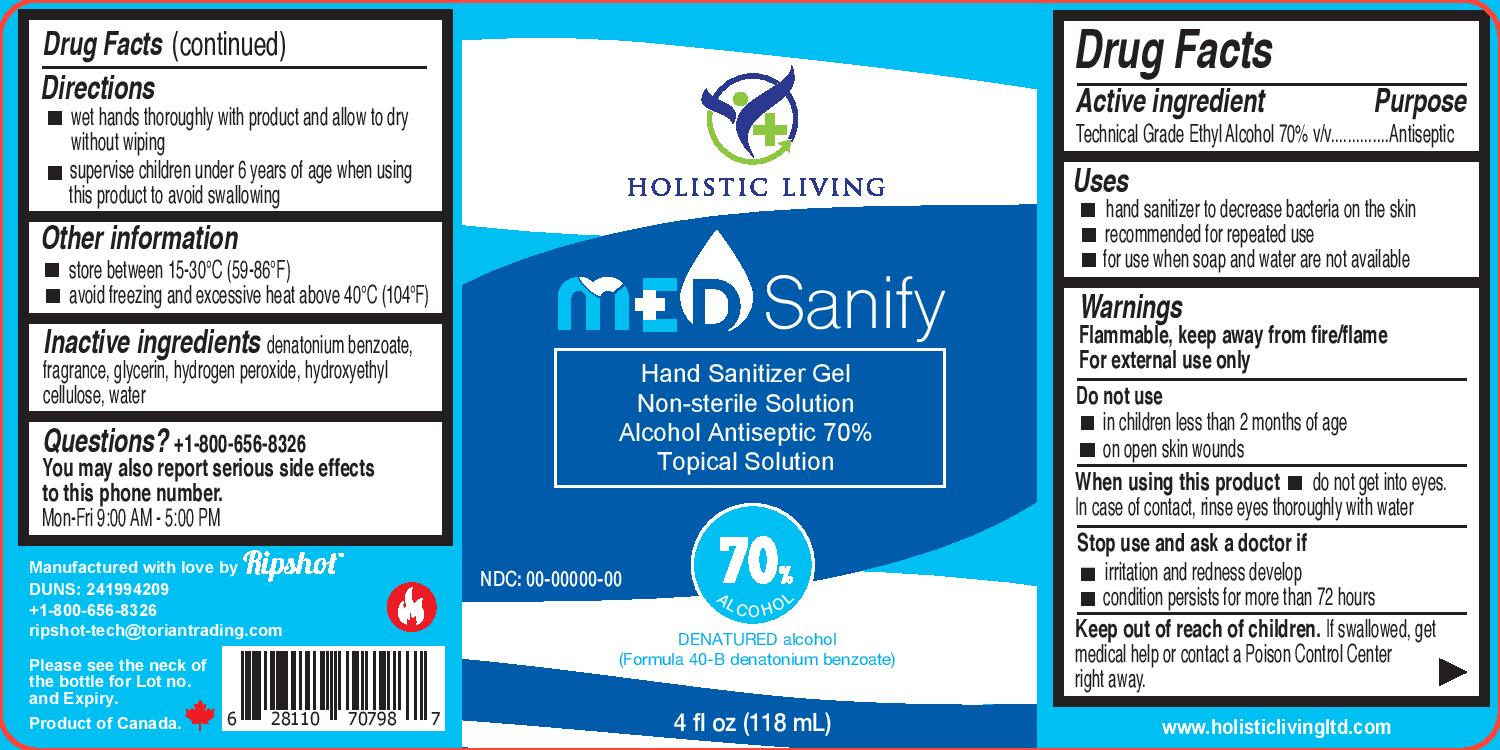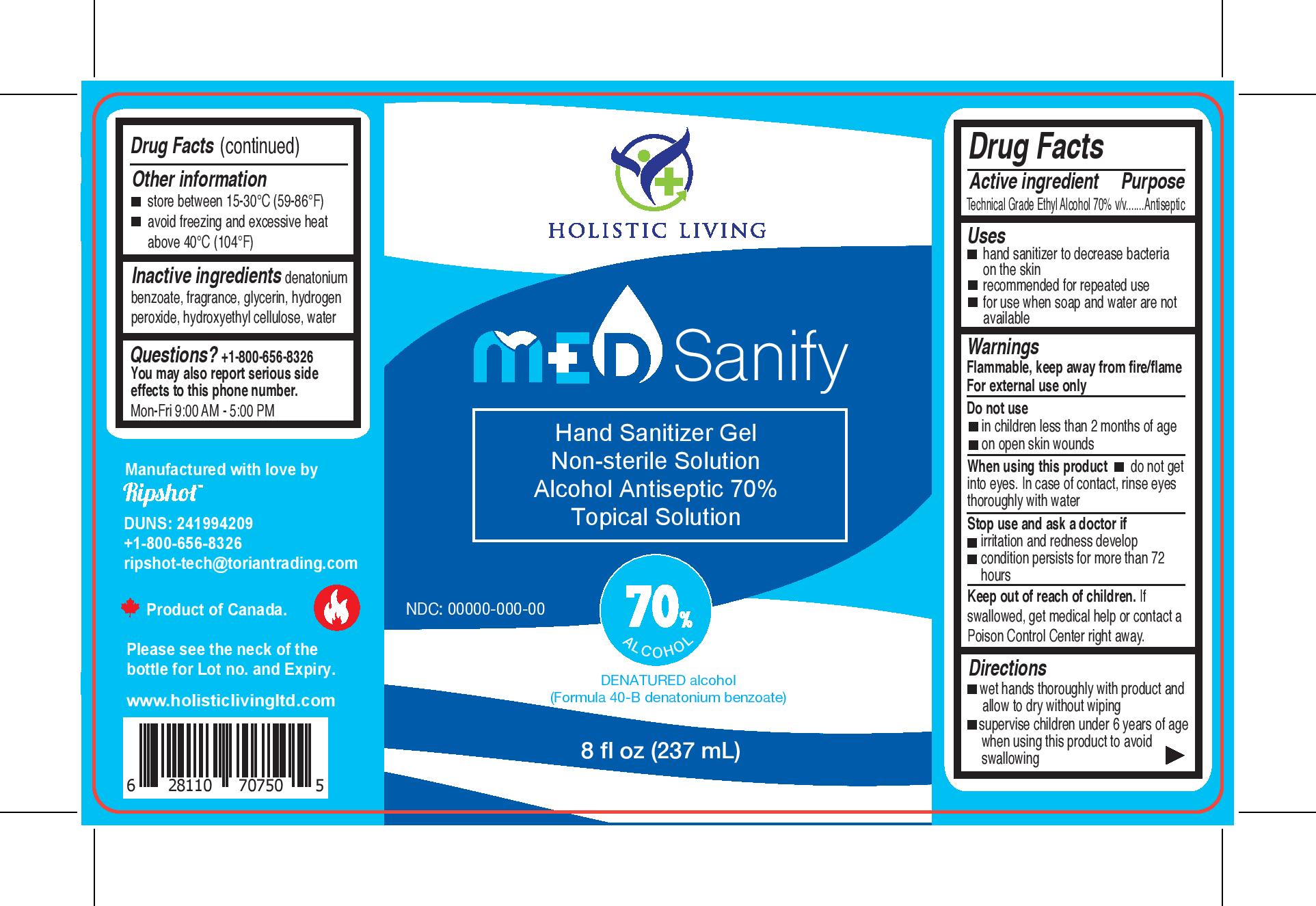 DRUG LABEL: Sanify
NDC: 78586-558 | Form: GEL
Manufacturer: Ripshot Enterprises
Category: otc | Type: HUMAN OTC DRUG LABEL
Date: 20200921

ACTIVE INGREDIENTS: ALCOHOL 71.351 mL/100 mL
INACTIVE INGREDIENTS: HYDROXYETHYL CELLULOSE (100 MPA.S AT 2%) 0.7027 mL/100 mL; GLYCERIN 0.8648 mL/100 mL; HYDROGEN PEROXIDE 0.1081 mL/100 mL; WATER 27.027 mL/100 mL

Hand Sanitizer

The hand sanitizer is manufactured using only the following ingredients in the preparation of the product (percentage in final product formulation).

1. Alcohol (ethanol) (71.35%, volume/volume (v/v)) in an aqueous solution denatured according to Alcohol and Tobacco Tax and Trade Bureau regulations in 27 CFR part 20.
2. Glycerol (0.8648% v/v).
3. Hydrogen peroxide (0.1081% v/v).
4. Hydroxyethyl cellulose
5. Sterile distilled water or boiled cold water.

The alcohol utilized in this formulation is consistent with the recommendations outlined in the Temporary Policy for Preparation of Certain Alcohol-Based Hand Sanitizer Products During the Public Health Emergency (COVID-19) Guidance for Industry

Active Ingredient(s)

Alcohol 80% v/v. Purpose: Antiseptic

Purpose

Antiseptic, Hand Sanitizer

Use

Hand Sanitizer to help reduce bacteria that potentially can cause disease. For use when soap and water are not available.

Warnings

For external use only. Flammable. Keep away from heat or flame

Do not use

- in children less than 2 months of age
- on open skin wounds

When using this product keep out of eyes, ears, and mouth. In case of contact with eyes, rinse eyes thoroughly with water.
Stop use and ask a doctor if irritation or rash occurs. These may be signs of a serious condition.
Keep out of reach of children. If swallowed, get medical help or contact a Poison Control Center right away.

Stop use and ask a doctor if irritation or rash occurs. These may be signs of a serious condition.

Keep out of reach of children. If swallowed, get medical help or contact a Poison Control Center right away.

Directions

- Place enough product on hands to cover all surfaces. Rub hands together until dry.
- Supervise children under 6 years of age when using this product to avoid swallowing.

Other information

- Store between 15-30C (59-86F)
- Avoid freezing and excessive heat above 40C (104F)

Inactive ingredients

glycerin, hydrogen peroxide, purified water,Hydroxyethyl cellulose

Package Label - Principal Display Panel

118mL NDC: 78586-558-04

236mL NDC: 78586-558-08

500mL NDC: 78586-558-69

1000mL NDC:78586-558-10